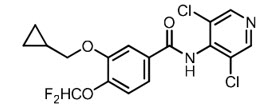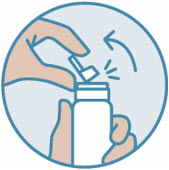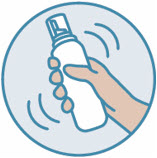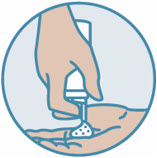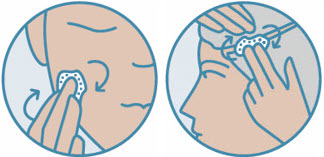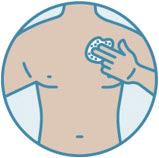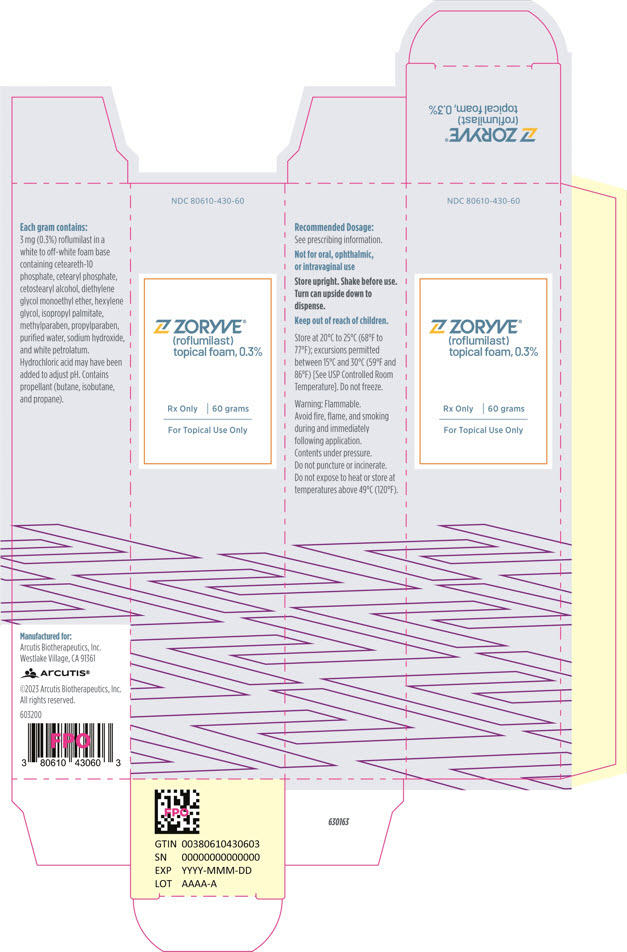 DRUG LABEL: ZORYVE
NDC: 80610-430 | Form: AEROSOL, FOAM
Manufacturer: Arcutis Biotherapeutics, Inc.
Category: prescription | Type: HUMAN PRESCRIPTION DRUG LABEL
Date: 20260130

ACTIVE INGREDIENTS: ROFLUMILAST 3 mg/1 g
INACTIVE INGREDIENTS: CETEARETH-10 PHOSPHATE; CETOSTEARYL ALCOHOL; CETEARYL PHOSPHATE; DIETHYLENE GLYCOL MONOETHYL ETHER; HEXYLENE GLYCOL; ISOPROPYL PALMITATE; METHYLPARABEN; PROPYLPARABEN; WATER; SODIUM HYDROXIDE; WHITE PETROLATUM; HYDROCHLORIC ACID; BUTANE; ISOBUTANE; PROPANE

HIGHLIGHTS OF PRESCRIBING INFORMATION

These highlights do not include all the information needed to use ZORYVE foam, 0.3%, safely and effectively. See full prescribing information for ZORYVE foam, 0.3%.
ZORYVE® (roflumilast) topical foam, 0.3%
Initial U.S. Approval: 2011

RECENT MAJOR CHANGES

Indications and Usage, Plaque Psoriasis (1.2) | 5/2025

1 INDICATIONS AND USAGE

ZORYVE topical foam, 0.3%, is a phosphodiesterase 4 inhibitor indicated for the treatment of

- seborrheic dermatitis in adult and pediatric patients 9 years of age and older. (1.1)
- plaque psoriasis of the scalp and body in adult and pediatric patients 12 years of age and older. (1.2)

2 DOSAGE AND ADMINISTRATION

- Apply once daily to affected areas. (2)
- For topical use only. Not for ophthalmic, oral, or intravaginal use. (2)

3 DOSAGE FORMS AND STRENGTHS

Topical foam, 0.3%: 3 mg of roflumilast per gram in 60-gram pressurized cans. (3)

4 CONTRAINDICATIONS

Moderate to severe liver impairment (Child-Pugh B or C). (4)

5 WARNINGS AND PRECAUTIONS

Flammability: The propellants in ZORYVE foam, 0.3%, are flammable. Avoid fire, flame, and smoking during and immediately following application. (5.1)

6 ADVERSE REACTIONS

The most common adverse reactions (reported in ≥ 1% of patients) are:

- Seborrheic dermatitis: nasopharyngitis, nausea, and headache. (6.1)
- Plaque psoriasis of the scalp and body: headache, diarrhea, nausea, and nasopharyngitis. (6.1)

To report SUSPECTED ADVERSE REACTIONS, contact Arcutis Biotherapeutics, Inc. at 1-844-692-6729 or FDA at 1-800-FDA-1088 or www.fda.gov/medwatch.

7 DRUG INTERACTIONS

- Co-administration of roflumilast with systemic CYP3A4 inhibitors or dual inhibitors that inhibit both CYP3A4 and CYP1A2 simultaneously may increase roflumilast systemic exposure and may result in increased adverse reactions. If these products are co-administered with ZORYVE foam, 0.3%, weigh the potential for increased adverse reactions against benefit. (7.1)
- Co-administration of roflumilast with oral contraceptives containing gestodene and ethinyl estradiol may increase roflumilast systemic exposure and may result in increased adverse reactions. If these products are co-administered with ZORYVE foam, 0.3%, weigh the potential for increased adverse reactions against benefit. (7.1)

FULL PRESCRIBING INFORMATION

1 INDICATIONS AND USAGE

1.1 Seborrheic Dermatitis

ZORYVE® topical foam, 0.3%, is indicated for the treatment of seborrheic dermatitis in adult and pediatric patients 9 years of age and older.

1.2 Plaque Psoriasis

ZORYVE topical foam, 0.3%, is indicated for the treatment of plaque psoriasis of the scalp and body in adult and pediatric patients 12 years of age and older.

2 DOSAGE AND ADMINISTRATION

Shake can prior to each use. Apply a thin layer of ZORYVE foam, 0.3%, once daily to affected areas of body and/or scalp when they are not wet. Rub in completely.

Wash hands after application.

Avoid fire, flame, and smoking during and immediately following application [see Warnings and Precautions (5.1)].

ZORYVE foam, 0.3%, is for topical use only and not for ophthalmic, oral, or intravaginal use.

3 DOSAGE FORMS AND STRENGTHS

Topical foam, 0.3%: 3 mg of roflumilast per gram of white to off-white foam in 60-gram pressurized cans.

4 CONTRAINDICATIONS

ZORYVE foam, 0.3%, is contraindicated in patients with moderate to severe liver impairment (Child-Pugh B or C) [see Use in Specific Populations (8.6), Clinical Pharmacology (12.3)].

5 WARNINGS AND PRECAUTIONS

5.1 Flammability

The propellants in ZORYVE foam, 0.3%, are flammable. Avoid fire, flame, and smoking during and immediately following application.

6 ADVERSE REACTIONS

6.1 Clinical Trials Experience

Because clinical trials are conducted under widely varying conditions, adverse reaction rates observed in the clinical trials of a drug cannot be directly compared to rates in the clinical trials of another drug and may not reflect the rates observed in practice.

Seborrheic Dermatitis

In two multicenter, randomized, double-blind, vehicle-controlled trials (Trial 203 and STRATUM), 683 adult and pediatric subjects 9 years of age or older with seborrheic dermatitis were treated with ZORYVE foam, 0.3%, or vehicle foam once daily for 8 weeks [see Clinical Studies (14.1)].

Table 1 presents adverse reactions that occurred in at least 1% of subjects treated with ZORYVE foam, 0.3%.

Table 1: Adverse Reactions Reported in ≥1% of Adult and Pediatric Subjects 9 Years of Age and Older with Seborrheic Dermatitis Treated with ZORYVE Foam, 0.3%, for 8 Weeks in Trial 203 and Trial STRATUM
Adverse Reaction | ZORYVE foam, 0.3% (N=458) n (%) | Vehicle foam (N=225) n (%)
Nasopharyngitis | 7 (1.5) | 1 (0.4)
Nausea | 6 (1.3) | 0 (0)
Headache | 5 (1.1) | 0 (0)

The following additional adverse reactions were reported in fewer than 1% of subjects treated with ZORYVE foam, 0.3%: diarrhea and insomnia.

The adverse reaction profile in pediatric subjects was consistent with that observed in adults [see Use in Specific Populations (8.4), Clinical Pharmacology (12.3)].

In 408 subjects who continued treatment with ZORYVE foam, 0.3%, for up to 24 to 52 weeks in an open-label, long-term trial, the adverse reaction profile was consistent with that observed in vehicle-controlled trials.

Plaque Psoriasis

In two multicenter, randomized, double-blind, vehicle-controlled trials (Trial 204 and ARRECTOR), 734 adult and pediatric subjects 12 years of age and older with plaque psoriasis of the scalp and body were treated with ZORYVE foam, 0.3%, or vehicle foam once daily for 8 weeks [see Clinical Studies (14.2)].

Table 2 presents adverse reactions that occurred in at least 1% of subjects treated with ZORYVE foam, 0.3%.

Table 2: Adverse Reactions Reported in ≥1% of Adult and Pediatric Subjects 12 Years of Age and Older with Plaque Psoriasis of the Scalp and Body Treated with ZORYVE Foam, 0.3%, for 8 Weeks in Trial 204 and Trial ARRECTOR
Adverse Reaction | ZORYVE foam, 0.3% (N=479) n (%) | Vehicle foam (N=255) n (%)
Headache | 15 (3.1) | 3 (1.2)
Diarrhea | 12 (2.5) | 4 (1.6)
Nausea | 8 (1.7) | 0 (0)
Nasopharyngitis | 6 (1.3) | 2 (0.8)

The following additional adverse reaction was reported in fewer than 1% of subjects treated with ZORYVE foam, 0.3%: insomnia.

The adverse reaction profile in pediatric subjects was consistent with that observed in adults [see Use in Specific Populations (8.4), Clinical Pharmacology (12.3)].

7 DRUG INTERACTIONS

7.1 Effects of Other Drugs on ZORYVE Foam, 0.3%

Drugs that Inhibit Cytochrome P450 (CYP) Enzymes

No formal drug-drug interaction studies were conducted with ZORYVE foam, 0.3%; however, the co-administration of oral roflumilast with systemic CYP3A4 inhibitors or dual inhibitors that inhibit both CYP3A4 and CYP1A2 simultaneously may increase roflumilast systemic exposure and may result in increased adverse reactions. If these products are co-administered with ZORYVE foam, 0.3%, weigh the potential for increased adverse reactions against benefit [see Clinical Pharmacology (12.3)].

Oral Contraceptives Containing Gestodene and Ethinyl Estradiol

The co-administration of roflumilast with oral contraceptives containing gestodene and ethinyl estradiol may increase roflumilast systemic exposure and may result in increased adverse reactions. If these products are co-administered with ZORYVE foam, 0.3%, weigh the potential for increased adverse reactions against benefit [see Clinical Pharmacology (12.3)].

8 USE IN SPECIFIC POPULATIONS

8.1 Pregnancy

Risk Summary

There are insufficient data available on the use of ZORYVE foam, 0.3%, in pregnant women to inform a drug-associated risk of major birth defects, miscarriage, or other adverse maternal or fetal outcomes. In animal reproduction studies, roflumilast administered orally to pregnant rats and rabbits during the period of organogenesis produced no fetal structural abnormalities at doses up to 21 and 18 times the maximum recommended human dose (MRHD), respectively. Roflumilast induced post-implantation loss in rats at oral doses greater than or equal to 7 times the MRHD. Roflumilast induced stillbirth and decreased pup viability in mice at oral doses 11 and 34 times the MRHD, respectively. Roflumilast has been shown to adversely affect pup post-natal development when dams were treated with an oral dose 34 times the MRHD during pregnancy and lactation periods in mice (see Data).

The background risk of major birth defects and miscarriage for the indicated population is unknown. In the U.S. general population, the estimated background risk of major birth defects and miscarriage in clinically recognized pregnancies is 2% to 4% and 15% to 20%, respectively.

Clinical Considerations

Labor and delivery

Avoid using ZORYVE foam, 0.3%, during labor and delivery. There are no human studies that have investigated effects of ZORYVE foam, 0.3%, on preterm labor or labor at term; however, animal studies showed that oral roflumilast disrupted the labor and delivery process in mice.

Data

Animal data

In an embryo-fetal development study, pregnant rats were dosed orally during the period of organogenesis with up to 1.8 mg/kg/day roflumilast (21 times the MRHD on a mg/m^2 basis). No evidence of structural abnormalities or effects on survival rates were observed. Roflumilast did not affect embryo-fetal development at a maternal oral dose of 0.2 mg/kg/day (2 times the MRHD on a mg/m^2 basis).

In a fertility and embryo-fetal development study, male rats were dosed orally with up to 1.8 mg/kg/day roflumilast for 10 weeks and females for 2 weeks prior to pairing and throughout the organogenesis period. Roflumilast induced pre- and post-implantation loss at maternal oral doses greater than or equal to 0.6 mg/kg/day (7 times the MRHD on a mg/m^2 basis). Roflumilast did not cause fetal structural abnormalities at maternal oral doses up to 1.8 mg/kg/day (20 times the MRHD on a mg/m^2 basis).

In an embryo-fetal development study in rabbits, pregnant does were dosed orally with 0.8 mg/kg/day roflumilast during the period of organogenesis. Roflumilast did not cause fetal structural abnormalities at the maternal oral doses of 0.8 mg/kg/day (18 times the MRHD on a mg/m^2 basis).

In pre- and post-natal developmental studies in mice, dams were dosed orally with up to 12 mg/kg/day roflumilast during the period of organogenesis and lactation. Roflumilast induced stillbirth and decreased pup viability at maternal oral doses greater than 2 mg/kg/day and 6 mg/kg/day, respectively (11 and 34 times the MRHD on a mg/m^2 basis, respectively). Roflumilast induced delivery retardation in pregnant mice at maternal oral doses greater than 2 mg/kg/day (11 times the MRHD on a mg/m^2 basis). Roflumilast decreased pup rearing frequencies at a maternal oral dose of 6 mg/kg/day during pregnancy and lactation (34 times the MRHD on a mg/m^2 basis). Roflumilast also decreased survival and forelimb grip reflex and delayed pinna detachment in mouse pups at a maternal oral dose of 12 mg/kg/day (68 times the MRHD on a mg/m^2 basis).

8.2 Lactation

Risk Summary

There are no data on the presence of roflumilast or its metabolite in human milk, the effects on the breastfed infant, or the effects on milk production.

Roflumilast and/or its metabolites are excreted into the milk of lactating rats (see Data). When a drug is present in animal milk, it is likely that the drug will be present in human milk. The developmental and health benefits of breastfeeding should be considered along with the mother's clinical need for ZORYVE foam, 0.3%, and any potential adverse effects on the breastfed infant from ZORYVE foam, 0.3%, or from the underlying maternal condition.

Clinical Considerations

To minimize potential exposure to the breastfed infant via breast milk, use ZORYVE foam, 0.3%, on the smallest area of skin and for the shortest duration possible while breastfeeding. To avoid direct infant exposure, advise breastfeeding women not to apply ZORYVE foam, 0.3%, directly to the nipple or areola. If applied to the patient's chest, avoid exposure via direct contact with the infant's skin.

Data

Animal data

Roflumilast and/or its metabolite concentrations measured 8 hours after an oral dose of 1 mg/kg given to lactating rats were 0.32 and 0.02 mcg/g in the milk and pup liver, respectively. The concentration of roflumilast in animal milk does not necessarily predict the concentration of drug in human milk.

8.3 Fertility

In a human spermatogenesis study, oral roflumilast 500 mcg had no effects on semen parameters or reproductive hormones during the 3-month treatment period and the following 3-month off-treatment period.

8.4 Pediatric Use

Seborrheic Dermatitis

The safety and effectiveness of ZORYVE topical foam, 0.3%, for the treatment of seborrheic dermatitis have been established in pediatric patients 9 years of age and older. Use of ZORYVE foam, 0.3%, in this age group is supported by data from two 8-week, vehicle-controlled trials which included 32 subjects 9 to 17 years of age, of whom 17 received ZORYVE foam, 0.3%, and from open-label trials of up to 52 weeks which included 23 pediatric subjects treated with ZORYVE foam, 0.3% [see Adverse Reactions (6.1), Clinical Pharmacology (12.3), Clinical Studies (14)].

The safety and effectiveness of ZORYVE foam, 0.3%, in pediatric patients below the age of 9 years have not been established.

Plaque Psoriasis

The safety and effectiveness of ZORYVE topical foam, 0.3%, for the treatment of plaque psoriasis of the scalp and body have been established in pediatric patients 12 years of age and older. Use of ZORYVE foam, 0.3%, in this age group is supported by data from two 8-week, vehicle-controlled trials which included 12 subjects 12 to 17 years of age, of whom 8 received ZORYVE foam, 0.3%. Use of ZORYVE foam, 0.3%, in pediatric patients 12 years of age and older is also supported by data from an open-label trial of 8 weeks duration which included 7 subjects 12 to 17 years of age treated with ZORYVE foam, 0.3%.

The safety and effectiveness of ZORYVE foam, 0.3%, in pediatric patients below the age of 12 years with plaque psoriasis have not been established.

8.5 Geriatric Use

Seborrheic Dermatitis

Of the 683 subjects with seborrheic dermatitis exposed to ZORYVE foam, 0.3%, or vehicle for up to 8 weeks in the controlled clinical trials, 98 (14%) were 65 years of age or older, and 33 (5%) were 75 years of age or older. No overall differences in safety or effectiveness were observed between these subjects and younger subjects, and other reported clinical experience has not identified differences in responses between the elderly and younger patients, but greater sensitivity of some older individuals cannot be ruled out.

Plaque Psoriasis

Of the 734 subjects with plaque psoriasis of the scalp and body exposed to ZORYVE foam, 0.3%, or vehicle for up to 8 weeks in the controlled clinical trials, 82 (11%) were 65 years of age or older, and 21 (3%) were 75 years of age or older. No overall differences in safety or effectiveness were observed between these subjects and younger subjects, and other reported clinical experience has not identified differences in responses between the elderly and younger patients, but greater sensitivity of some older individuals cannot be ruled out.

8.6 Hepatic Impairment

Oral roflumilast 250 mcg once daily for 14 days was studied in subjects with hepatic impairment. The systemic exposure of roflumilast and roflumilast N-oxide were increased in subjects with moderate (Child-Pugh B) hepatic impairment. ZORYVE foam, 0.3%, is contraindicated in patients with moderate to severe liver impairment (Child-Pugh B or C). No dosage adjustment is needed in patients with mild (Child-Pugh A) hepatic impairment [see Contraindications (4), Clinical Pharmacology (12.3)].

11 DESCRIPTION

ZORYVE (roflumilast) topical foam, 0.3%, is a white to off-white foam for topical use. The active ingredient, roflumilast, is a phosphodiesterase 4 (PDE4) inhibitor.

The chemical name of roflumilast is 3-cyclopropylmethoxy-N-(3,5-dichloropyridin-4-yl)-4-(difluoromethoxy)benzamide with a molecular formula of C17H14Cl2F2N2O3 and the molecular weight of 403.21.

The structural formula of roflumilast is:

Roflumilast is practically insoluble in water and hexane, sparingly soluble in ethanol, and freely soluble in acetone.

Each gram of ZORYVE topical foam, 0.3%, contains 3 mg of roflumilast in a foam base containing ceteareth-10 phosphate, cetearyl phosphate, cetostearyl alcohol, diethylene glycol monoethyl ether, hexylene glycol, isopropyl palmitate, methylparaben, propylparaben, purified water, sodium hydroxide, and white petrolatum. Hydrochloric acid may have been added to adjust pH. ZORYVE topical foam, 0.3%, is dispensed from an aluminum can pressurized with propellant (butane, isobutane, and propane).

12 CLINICAL PHARMACOLOGY

12.1 Mechanism of Action

Roflumilast and its active metabolite (roflumilast N-oxide) are inhibitors of PDE4. Roflumilast and roflumilast N-oxide inhibition of PDE4 (a major cyclic 3′,5′-adenosine monophosphate (cyclic AMP) metabolizing enzyme) activity leads to accumulation of intracellular cyclic AMP. The specific mechanism(s) by which roflumilast exerts its therapeutic action is not well defined.

12.2 Pharmacodynamics

Pharmacodynamics of ZORYVE foam, 0.3%, in the treatment of seborrheic dermatitis and plaque psoriasis is unknown.

12.3 Pharmacokinetics

Absorption

Seborrheic Dermatitis

The pharmacokinetics of ZORYVE foam, 0.3%, was investigated in 10 adult and 10 pediatric (11 to 16 years of age) subjects with seborrheic dermatitis. In this study, a mean dose of approximately 4.1 g of ZORYVE foam, 0.3%, was applied once daily for 15 days to a mean ± SD body surface area (BSA) involvement of 6.5 ± 1.08% and 5.5 ± 1.27% in adult and pediatric subjects, respectively. Plasma concentrations of roflumilast were quantifiable in all but two subjects at Day 15. Plasma concentrations of roflumilast N-oxide were quantifiable in all subjects at Day 15. Following application of ZORYVE foam, 0.3%, the plasma concentration versus time profile was relatively flat, with mean peak-to-trough ratios of 1.68 and 1.62 for roflumilast and roflumilast N-oxide, respectively.

In adults, the mean ± SD maximum concentration (Cmax) was 2.2 ± 1.6 and 13.8 ± 9.0 ng/mL for roflumilast and the N-oxide metabolite, respectively. The mean ± SD systemic exposure (AUC0-24) was 36.6 ± 23.7 and 261 ± 190 h∙ng/mL for roflumilast and the N-oxide metabolite, respectively. In pediatric subjects, the extrapolated mean ± SD AUC0-24 (based on pre-dose concentration) was 25.1 ± 30.2 and 253 ± 404 h∙ng/mL for roflumilast and the N-oxide metabolite, respectively.

Plaque Psoriasis

The pharmacokinetics of ZORYVE foam, 0.3%, was investigated in 19 adults and 7 pediatric subjects 12 to 16 years of age with plaque psoriasis of the scalp and body. The entire scalp (BSA of approximately 4.5%) was treated in addition to the mean ± SD BSA involvement on the body of 25.0 ± 7.88% and 10.4 ± 0.54% in adults and pediatric subjects, respectively. In this study, the mean daily dose administered in adults was 10.3 g and in pediatric subjects from 12 to 16 years of age was 5.3 g of ZORYVE foam, 0.3%, once daily for 15 days. Following application of ZORYVE foam, 0.3%, the plasma concentration versus time profile was flat, with mean peak-to-trough ratios of approximately 1.2 for both roflumilast and roflumilast N-oxide.

In adults, the mean ± SD Cmax was 4.48 ± 2.28 and 29.9 ± 17.5 ng/mL for roflumilast and the N-oxide metabolite, respectively, on Day 15. The mean ± SD AUC0-24 was 90 ± 58.7 and 567 ± 436 h∙ng/mL for roflumilast and the N-oxide metabolite, respectively, on Day 15. In pediatric subjects, the extrapolated mean ± SD AUC0-24 (based on pre-dose concentration) was 35.5 ± 41.4 and 270 ± 293 h∙ng/mL for roflumilast and the N-oxide metabolite, respectively, on Day 15.

Distribution

Plasma protein binding of roflumilast and its N-oxide metabolite is approximately 99% and 97%, respectively.

Elimination

The plasma clearance after short-term intravenous infusion of roflumilast is on average about 9.6 L/h. Following topical administration, the mean half-lives of both roflumilast and the N-oxide metabolite were in the range of 3.6 to 5 days.

Metabolism

Roflumilast is extensively metabolized via Phase I (cytochrome P450) and Phase II (conjugation) reactions. The N-oxide metabolite is the only major metabolite observed in the plasma of humans. Following oral administration, roflumilast and roflumilast N-oxide account for the majority (87.5%) of total dose administered in plasma. Roflumilast was not detectable in urine, while roflumilast N-oxide was only a trace metabolite (less than 1%). Other conjugated metabolites such as roflumilast N-oxide glucuronide and 4-amino-3,5-dichloropyridine N-oxide were detected in urine.

While roflumilast is 3 times more potent than roflumilast N-oxide at inhibition of the PDE4 enzyme in vitro, the plasma AUC of roflumilast N-oxide on average is approximately 7-fold greater than the plasma AUC of roflumilast following topical administration. A similar ratio was observed following intravenous administration, whereas following oral administration the N-oxide metabolite circulated on average about 10-fold higher than the parent drug.

Specific Populations

Following topical administration, no clinically significant differences in the pharmacokinetics of roflumilast and roflumilast N-oxide were observed based on age, sex, race, or ethnicity.

Patients with Hepatic Impairment

No studies were conducted with topical roflumilast in subjects with hepatic impairment; however, oral roflumilast 250 mcg once daily for 14 days was studied in subjects with mild to moderate hepatic impairment classified as Child-Pugh A and B (8 subjects in each group). The AUC of roflumilast and roflumilast N-oxide were increased by 51% and 24%, respectively, in Child-Pugh A subjects and by 92% and 41%, respectively, in Child-Pugh B subjects, as compared to age-, weight-, and gender-matched healthy subjects. The Cmax of roflumilast and roflumilast N-oxide were increased by 3% and 26%, respectively, in Child-Pugh A subjects and by 26% and 40%, respectively, in Child-Pugh B subjects, as compared to healthy subjects [see Contraindications (4)].

Patients with Renal Impairment

No studies were conducted with topical roflumilast in subjects with renal impairment. Following oral administration in 12 subjects with severe renal impairment, no clinically significant differences in the pharmacokinetics of roflumilast and roflumilast N-oxide were observed.

Drug Interaction Studies

Clinical Studies

No formal drug-drug interaction studies were conducted with roflumilast topical foam, 0.3%.

Since a major step in roflumilast metabolism is the N-oxidation of roflumilast to roflumilast N-oxide by CYP3A4 and CYP1A2, drug interaction studies were performed with oral roflumilast and systemic inhibitors of CYP3A4 and CYP1A2 [see Drug Interactions (7)].

Erythromycin: In an open-label crossover study in 16 healthy volunteers, the co-administration of CYP3A4 inhibitor erythromycin (500 mg 3 times daily for 13 days) with a single oral dose of 500 mcg roflumilast resulted in 40% and 70% increase in Cmax and AUC for roflumilast, respectively, and a 34% decrease and a 4% increase in Cmax and AUC for roflumilast N-oxide, respectively.

Ketoconazole: In an open-label crossover study in 16 healthy volunteers, the co-administration of a strong CYP3A4 inhibitor ketoconazole (200 mg twice daily for 13 days) with a single oral dose of 500 mcg roflumilast resulted in 23% and 99% increase in Cmax and AUC for roflumilast, respectively, and a 38% reduction and 3% increase in Cmax and AUC for roflumilast N-oxide, respectively.

Fluvoxamine: In an open-label crossover study in 16 healthy volunteers, the co-administration of dual CYP 3A4/1A2 inhibitor fluvoxamine (50 mg daily for 14 days) with a single oral dose of 500 mcg roflumilast showed a 12% and 156% increase in roflumilast Cmax and AUC along with a 210% decrease and 52% increase in roflumilast N-oxide Cmax and AUC, respectively.

Enoxacin: In an open-label crossover study in 16 healthy volunteers, the co-administration of dual CYP 3A4/1A2 inhibitor enoxacin (400 mg twice daily for 12 days) with a single oral dose of 500 mcg roflumilast resulted in an increased Cmax and AUC of roflumilast by 20% and 56%, respectively. Roflumilast N-oxide Cmax was decreased by 14% while roflumilast N-oxide AUC was increased by 23%.

Cimetidine: In an open-label crossover study in 16 healthy volunteers, the co-administration of a dual CYP 3A4/1A2 inhibitor cimetidine (400 mg twice daily for 7 days) with a single oral dose of 500 mcg roflumilast resulted in a 46% and 85% increase in roflumilast Cmax and AUC; and a 4% decrease in Cmax and 27% increase in AUC for roflumilast N-oxide, respectively.

Oral Contraceptives Containing Gestodene and Ethinyl Estradiol: In an open-label crossover study in 20 healthy adult volunteers, co-administration of a single oral dose of roflumilast with repeated doses of a fixed combination oral contraceptive containing 0.075 mg gestodene and 0.03 mg ethinyl estradiol to steady state caused a 38% increase and 12% decrease in Cmax of roflumilast and roflumilast N-oxide, respectively. Roflumilast and roflumilast N-oxide AUCs were increased by 51% and 14%, respectively.

In Vitro Studies

Cytochrome P450 (CYP) Enzymes: In vitro studies suggest that the biotransformation of roflumilast to its N-oxide metabolite is mediated by CYP1A2 and 3A4. Based on further in vitro results in human liver microsomes, roflumilast and roflumilast N-oxide therapeutic plasma concentrations do not inhibit CYP1A2, 2A6, 2B6, 2C8, 2C9, 2C19, 2D6, 2E1, 3A4/5, or 4A9/11; therefore, there is a low probability of relevant interactions with substances metabolized by these P450 enzymes. In addition, in vitro studies demonstrated no induction of the CYP1A2, 2A6, 2C9, 2C19, or 3A4/5 and only a weak induction of CYP2B6 by roflumilast.

13 NONCLINICAL TOXICOLOGY

13.1 Carcinogenesis, Mutagenesis, Impairment of Fertility

Long-term studies were conducted in hamsters and mice with roflumilast to evaluate its carcinogenic potential. In 2-year oral gavage carcinogenicity studies, roflumilast treatment resulted in dose-related, statistically significant increases in the incidence of undifferentiated carcinomas of nasal epithelium in hamsters at doses greater than or equal to 8 mg/kg/day (11 times the MRHD on an AUC basis). The tumorigenicity of roflumilast appears to be attributed to a reactive metabolite of 4-amino-3,5-dichloropyridine N-oxide (ADCP N-oxide). No evidence of tumorigenicity was observed in mice at roflumilast oral doses up to 12 and 18 mg/kg/day in females and males, respectively (10 and 15 times the MRHD, respectively, on an AUC basis).

In a 2-year dermal mouse carcinogenicity study, no evidence of carcinogenicity was observed at topical doses of roflumilast cream up to 1% applied at 2 mL/kg/day (4 times the MRHD on an AUC basis).

Roflumilast tested positive in an in vivo mouse micronucleus test, but negative in the following assays: the Ames test, an in vitro chromosome aberration assay in human lymphocytes, an in vitro HPRT assay with V79 cells, an in vitro micronucleus test with V79 cells, a DNA adduct formation assay in rat nasal mucosa, liver, and testes, and an in vivo mouse bone marrow chromosome aberration assay. Roflumilast N-oxide was negative in the Ames test and an in vitro micronucleus test with V79 cells.

In a fertility study, oral roflumilast decreased fertility rates in male rats at 1.8 mg/kg/day (20 times the MRHD on a mg/m^2 basis). The male rats also showed increases in the incidence of tubular atrophy, degeneration in the testis, and spermiogenic granuloma in the epididymides. No effect on rat fertility rate or male reproductive organ morphology was observed at 0.6 mg/kg/day (7 times the MRHD on a mg/m^2 basis). In a female fertility study, no effect on fertility was observed up to the highest roflumilast dose of 1.5 mg/kg/day in rats (17 times the MRHD on a mg/m^2 basis).

14 CLINICAL STUDIES

14.1 Seborrheic Dermatitis

Two randomized, double-blind, vehicle-controlled trials (STRATUM [NCT04973228] and Trial 203 [NCT04091646]) enrolled a total of 683 adult and pediatric subjects with seborrheic dermatitis involving the scalp, face, and/or body with an Investigator Global Assessment (IGA) of moderate or severe (IGA of 3 or 4 on a 5-point scale from 0 to 4). In each trial, subjects were randomized 2:1 to receive ZORYVE foam, 0.3%, or vehicle foam applied once daily for 8 weeks. The combined trial population was 50% male, 79% White, 11% Black, 5% Asian, and 5% other races; for ethnicity, 79% identified as non-Hispanic/Latino and 21% identified as Hispanic/Latino. In Trial STRATUM, the trial population ranged in age from 9 to 87 years, including 7% of subjects who were 9 to 17 years of age and 12% of subjects who were 65 years of age or older. At baseline, 94% of subjects had an IGA score of 3 (moderate), and 6% had an IGA score of 4 (severe). At baseline, 67% of subjects had a Worst Itch-Numeric Rating Scale (WI-NRS) score of 4 or higher on a scale of 0 to 10. In Trial 203, the trial population ranged in age from 18 to 85 years, including 18% who were 65 years of age or older. At baseline, 93% of subjects had an IGA score of 3 (moderate), and 7% had an IGA score of 4 (severe). At baseline, 81% of subjects had a Worst Itch-Numeric Rating Scale (WI-NRS) score of 4 or higher on a scale of 0 to 10.

The primary endpoint was the proportion of subjects who achieved IGA treatment success at Week 8 (Table 3). Success was defined as a score of "Clear" (0) or "Almost Clear" (1), plus a 2-grade improvement from baseline.

Table 3: IGA Treatment Success at Week 8 in Adult and Pediatric Subjects 9 Years of Age and Older with Moderate to Severe Seborrheic Dermatitis in Trial STRATUM and Trial 203
 | STRATUM |  | Trial 203
 | ZORYVE foam, 0.3% | Vehicle foam | ZORYVE foam, 0.3% | Vehicle foam
Number of subjects randomized | N=304 | N=153 | N=154 | N=72
IGA success [IGA treatment success was defined as an IGA score of "Clear" (0) or "Almost Clear" (1), plus a 2-grade IGA score improvement from baseline at Week 8 (Multiple Imputation).] | 79.5% | 58.0% | 73.1% | 40.8%
Difference from Vehicle (95% CI) [Treatment difference and 95% CI are based on the CMH method stratified by pooled site and baseline IGA strata.] | 20.6% (11.2%, 30.0%) |  | 33.8% (20.3%, 47.4%)
Abbreviations: CI = Confidence Interval

In Trial STRATUM, among subjects with a baseline WI-NRS score of at least 4 (67% of subjects), there was a higher percentage of subjects who achieved a reduction of at least 4 points from baseline at Week 8 in the group who received ZORYVE foam, 0.3%, compared to the group who received vehicle foam (62.8% vs. 40.6% for a treatment difference of 25.7% and 95% CI of (13.4, 38.1)).

14.2 Plaque Psoriasis

Two randomized, double-blind, vehicle-controlled trials (ARRECTOR [NCT05028582] and Trial 204 [NCT04128007]) enrolled a total of 736 adult and pediatric subjects 12 years of age and older with mild to severe plaque psoriasis of the scalp and body. In each trial, subjects were randomized 2:1 to receive ZORYVE foam, 0.3%, or vehicle foam applied once daily for 8 weeks. The combined trial population was 55% female, 85% White, 5% Black, 6% Asian, and 4% other races; for ethnicity, 79% identified as non-Hispanic/Latino and 19% identified as Hispanic/Latino. The median age was 47 years (range 12 to 87 years).

In Trial ARRECTOR, the trial population ranged in age from 12 to 87 years, including 2% of subjects who were 12 to 17 years of age and 13% of subjects who were 65 years of age or older. At baseline, 86% of subjects had a Scalp Investigator Global Assessment (S-IGA) score of 3 (moderate) on a 5-point scale of 0 to 4, and 14% had an S-IGA score of 4 (severe); 28% of subjects had a Body Investigator Global Assessment (B-IGA) score of 2 (mild), 67% of subjects had a B-IGA score of 3 (moderate), and 5% had a B-IGA score of 4 (severe). At baseline, 76% of subjects had a Scalp Itch-Numeric Rating Scale (SI-NRS) score of 4 or higher on a scale of 0 to 10 and 73% had a Worst Itch-Numeric Rating Scale (WI-NRS) score of 4 or higher.

In Trial 204, the trial population ranged in age from 12 to 87 years, including 1% of subjects who were 12 to 17 years of age, and 9% who were 65 years of age or older. At baseline, 11% of subjects had an S-IGA score of 2 (mild), 76% of subjects had an S-IGA score of 3 (moderate), and 13% had an S-IGA score of 4 (severe); 36% of subjects had a B-IGA score of 2 (mild), 59% of subjects had a B-IGA score of 3 (moderate), and 5% had a B-IGA score of 4 (severe). At baseline, 89% of subjects had an SI-NRS score of 4 or higher on a scale of 0 to 10.

In both trials, S-IGA treatment success, a primary endpoint in ARRECTOR and Trial 204, and B-IGA treatment success, a primary endpoint in ARRECTOR, were defined as a score of "Clear" (0) or "Almost Clear" (1), plus a 2-grade improvement from baseline.

Table 4: S-IGA and B-IGA Treatment Success at Week 8 in Adult and Pediatric Subjects 12 Years of Age and Older with Plaque Psoriasis of the Scalp and Body in Trial ARRECTOR and Trial 204
 | Trial ARRECTOR |  | Trial 204
 | ZORYVE foam, 0.3% | Vehicle foam | ZORYVE foam, 0.3% | Vehicle foam
Number of subjects randomized | N=281 | N=151 | N=200 | N=104
S-IGA success [S-IGA treatment success and B-IGA treatment success were defined as a score of "Clear" (0) or "Almost Clear" (1), plus a 2-grade score improvement from baseline at Week 8 (Multiple Imputation).] | 66.4% | 27.8% | 56.7% | 11.0%
Difference from Vehicle (95% CI) [Treatment difference and 95% CI are based on the CMH method stratified by pooled site and baseline IGA strata.] | 37.1% (27.1%, 47.1%) |  | 47.7% (37.9%, 57.5%)
B-IGA success | 45.5% | 20.1% | 39.0% | 7.4%
Difference from Vehicle (95% CI) | 24.8% (15.0%, 34.6%) |  | 32.4% (23.3%, 41.6%)
Abbreviations: CI = Confidence Interval

SI-NRS success and WI-NRS success were defined as a reduction of at least 4 points from baseline with a baseline score of at least 4. In Trial ARRECTOR, among subjects with a baseline SI-NRS score of at least 4 (75% of subjects), a higher percentage of subjects achieved SI-NRS success at Week 8 in the group who received ZORYVE foam, 0.3%, compared to the group who received vehicle foam (65.3% vs. 30.3% for a treatment difference of 35.4% and 95% CI of (23.9, 47.0)). In Trial ARRECTOR, among subjects with a baseline WI-NRS score of at least 4 (72% of subjects), a higher percentage of subjects achieved WI-NRS success at Week 8 in the group who received ZORYVE foam, 0.3%, compared to the group who received vehicle foam (63.1% vs. 30.1% for a treatment difference of 32.8% and 95% CI of (20.3, 45.2)).

16 HOW SUPPLIED/STORAGE AND HANDLING

How Supplied

ZORYVE (roflumilast) topical foam, 0.3%, is a white to off-white foam. It is supplied in a 60-gram pressurized aluminum can (NDC 80610-430-60).

Storage and Handling

Store at 20°C to 25°C (68°F to 77°F); excursions permitted between 15°C and 30°C (59°F and 86°F) [See USP Controlled Room Temperature].

Do not freeze.

Store upright.

Flammable. Contents under pressure. Do not puncture or incinerate. Do not expose to heat or store at temperatures above 49°C (120°F) [see Warnings and Precautions (5.1)].

17 PATIENT COUNSELING INFORMATION

Advise the patient or caregiver to read the FDA-approved patient labeling (Patient Information).

Administration Instructions

Advise patients or caregivers that ZORYVE foam, 0.3%, is for topical use only and is not for ophthalmic, oral, or intravaginal use [see Dosage and Administration (2)].

Instruct patients or caregivers to shake the can of ZORYVE foam, 0.3%, prior to each use [see Dosage and Administration (2)].

Instruct patients or caregivers to wash hands after applying ZORYVE foam, 0.3% [see Dosage and Administration (2)].

Flammability

Because the propellants in ZORYVE foam, 0.3%, are flammable, instruct the patient to avoid fire, flame, and smoking during and immediately following application [see Dosage and Administration (2), Warnings and Precautions (5.1)].

Lactation

Advise patients to use ZORYVE foam, 0.3%, on the smallest area of skin and for the shortest duration possible while breastfeeding. Instruct patients who are breastfeeding not to apply ZORYVE foam, 0.3%, directly to the nipple or areola to avoid direct infant exposure. Instruct patients to avoid inadvertent contact of treated areas with infant skin [see Use in Specific Populations (8.2)].

Marketed by:
Arcutis Biotherapeutics, Inc.
Westlake Village, CA 91361

For more information on ZORYVE foam, call 1-805-418-5006 or visit http://www.zoryve.com.

© 2025 Arcutis Biotherapeutics, Inc. All rights reserved.

v2

Patient Information
ZORYVE® (zor-EEV)
(roflumilast) topical foam, 0.3%

Important information: ZORYVE foam is for use on the skin (topical use) only. Do not use ZORYVE foam in or on your eyes, mouth, or vagina.

What is ZORYVE foam?
ZORYVE foam is a prescription medicine used on the skin (topical) to treat:

- seborrheic dermatitis in adults and children 9 years of age and older.
  It is not known if ZORYVE foam is safe and effective in children with seborrheic dermatitis under 9 years of age.
- plaque psoriasis of the scalp and body in adults and children 12 years of age and older.
  It is not known if ZORYVE foam is safe and effective in children with plaque psoriasis of the scalp and body under 12 years of age.

Do not use ZORYVE foam if you have certain liver problems.

Before using ZORYVE foam, tell your healthcare provider about all of your medical conditions, including if you:

- have liver problems.
- are pregnant or plan to become pregnant. It is not known if ZORYVE foam will harm your unborn baby.
- are breastfeeding or plan to breastfeed. It is not known if ZORYVE foam passes into your breast milk. Talk to your healthcare provider about the best way to feed your baby during treatment with ZORYVE foam.
  Breastfeeding women using ZORYVE foam should use it on the smallest area of the skin and for the shortest time needed. Do not apply ZORYVE foam directly to the nipple or areola to avoid contact with your baby. Avoid direct skin contact of treated areas with your baby if ZORYVE foam is applied to your chest.

Tell your healthcare provider about the medicines you take, including prescription and over-the-counter medicines, vitamins, and herbal supplements.

How should I use ZORYVE foam?

- Use ZORYVE foam exactly as your healthcare provider tells you to use it. See the "Instructions for Use" provided with this leaflet for directions about how to apply ZORYVE foam.
- Shake the can of ZORYVE foam before each use.
- Apply a thin layer of ZORYVE foam 1 time a day to the affected areas of your body and scalp when they are not wet. Rub the foam in completely.
- Wash your hands after applying ZORYVE foam. If someone else applies ZORYVE foam for you, they should wash their hands after applying it.

What should I avoid while using ZORYVE foam?
ZORYVE foam is flammable. Avoid fire, flame, and smoking during and right after you apply ZORYVE foam.

What are the possible side effects of ZORYVE foam?
The most common side effects of ZORYVE foam in people treated for seborrheic dermatitis include:

- common cold
- nausea
- headache

The most common side effects of ZORYVE foam in people treated for plaque psoriasis include:

- headache
- diarrhea
- nausea
- common cold

These are not all of the possible side effects of ZORYVE foam.
Call your doctor for medical advice about side effects. You may report side effects to FDA at 1-800-FDA-1088.
You may also report side effects to Arcutis Biotherapeutics, Inc. by calling 1-844-692-6729.

How should I store ZORYVE foam?

- Store ZORYVE foam at room temperature between 68°F to 77°F (20°C to 25°C).
- ZORYVE foam is flammable. Keep away from heat and flame.
- The contents in ZORYVE foam are under pressure. Do not puncture or burn the can. Do not expose the can to heat or store at temperatures above 120°F (49°C).
- Do not freeze.
- Store the can upright.

Keep ZORYVE foam and all medicines out of the reach of children.

General Information about the safe and effective use of ZORYVE foam.
Medicines are sometimes prescribed for purposes other than those listed in a Patient Information leaflet. Do not use ZORYVE foam for a condition for which it was not prescribed. Do not give it to other people, even if they have the same symptoms that you have. It may harm them. You can ask your pharmacist or healthcare provider for information about ZORYVE foam that is written for health professionals.

What are the ingredients in ZORYVE foam?
Active ingredient: roflumilast
Inactive ingredients: ceteareth-10 phosphate, cetearyl phosphate, cetostearyl alcohol, diethylene glycol monoethyl ether, hexylene glycol, isopropyl palmitate, methylparaben, propylparaben, purified water, sodium hydroxide, and white petrolatum. Hydrochloric acid may have been added to adjust pH.
Propellants: butane, isobutane, and propane.
Marketed by:
Arcutis Biotherapeutics, Inc.
Westlake Village, CA 91361
For more information on ZORYVE topical foam, call 1-844-692-6729 or visit http://www.zoryve.com.

This Patient Information has been approved by the U.S. Food and Drug Administration.

Revised: 5/2025

v2

INSTRUCTIONS FOR USE ZORYVE® (zor-EEV) (roflumilast) topical foam, 0.3%

This Instructions for Use contains information on how to apply ZORYVE foam.

Read this Instructions for Use before you start using ZORYVE foam and each time you get a refill. There may be new information. This information does not take the place of talking with your healthcare provider about your medical condition or treatment. Use ZORYVE foam exactly as your healthcare provider tells you.

Important information you need to know before applying ZORYVE foam:

- ZORYVE foam is for use on skin only (topical use). ZORYVE foam is not for use in your eyes, mouth, or vagina.
- ZORYVE foam is flammable. Avoid fire, flame, and smoking during and right after you apply ZORYVE foam.

Before applying ZORYVE foam for the first time:

Gently pull back on the nozzle to break the plastic piece at the base.

Applying ZORYVE foam:

Apply a thin layer of ZORYVE foam 1 time a day to the affected areas of your body and scalp when they are not wet.

Step 1: Shake.

- Shake the can well before each use.

Step 2: Dispense.

- Turn the can upside down and press the nozzle.
- Dispense a small amount into your hand.

Step 3: Apply.

- Use enough ZORYVE foam to cover all affected areas with a thin layer. Rub the foam in completely.
- If you are treating your scalp, part the hair so that ZORYVE foam can be applied directly to the affected area on the skin.
- Wash your hands after applying the medicine. If someone else applies ZORYVE foam for you, they should wash their hands after applying it.

Storing ZORYVE foam

- Store ZORYVE foam at room temperature between 68°F to 77°F (20°C to 25°C).
- ZORYVE foam is flammable. Keep away from heat and flame.
- The contents in ZORYVE foam are under pressure. Do not puncture or burn the can. Do not expose the can to heat or store at temperatures above 120°F (49°C).
- Do not freeze.
- Store the can upright.

Keep ZORYVE foam and all medicines out of the reach of children.

Marketed by:
Arcutis Biotherapeutics, Inc.
Westlake Village, CA 91361

For more information on ZORYVE foam, call 1-844-692-6729 or visit http://www.zoryve.com.

This Instructions for Use has been approved by the U.S. Food and Drug Administration.

Revised: 5/2025

v2

PRINCIPAL DISPLAY PANEL - 60 g Can Carton

NDC 80610-430-60

ZORYVE®
(roflumilast)
topical foam, 0.3%

Rx Only
60 grams

For Topical Use Only